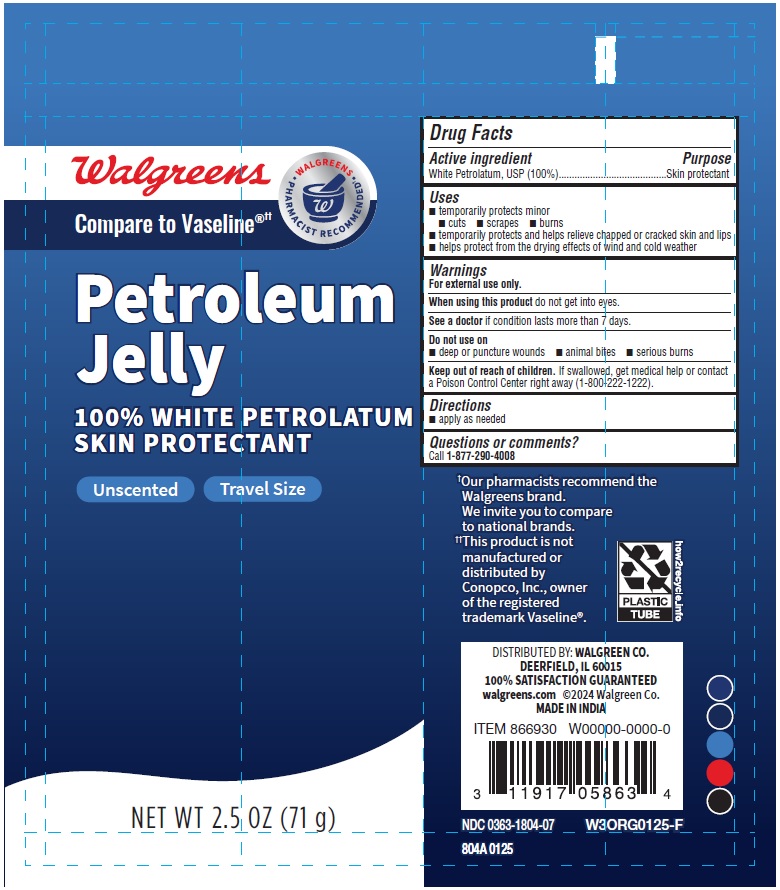 DRUG LABEL: Petroleum Jelly
NDC: 0363-1804 | Form: JELLY
Manufacturer: WALGREENS
Category: otc | Type: HUMAN OTC DRUG LABEL
Date: 20250531

ACTIVE INGREDIENTS: WHITE PETROLATUM 100 g/100 g

804A - Walgreens- Petroleum Jelly 2.5 oz tube

Drug Facts

Active ingredient

White Petrolatum, USP (100%)

Purpose

Skin protectant

Uses

- temporarily protects minor

- cuts
- scrapes
- burns

- temporarily protects and helps relieve chapped or cracked skin and lips
- helps protect from the drying effects of wind and cold weather

Warnings

For external use only.

When using this product do not get into eyes.

ASK DOCTOR

See a doctor if condition lasts more than 7 days.

Do not use on

- deep or puncture wounds
- animal bites
- serious burns

Keep out of reach of children. If swallowed, get medical help or contact a Poison Control Center right away (1-800-222-1222).

Directions

- apply as needed

Questions or comments?Call 1-877-290-4008

Inactive Ingredients -